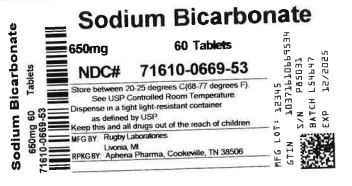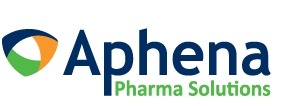 DRUG LABEL: Sodium Bicarbonate Antacid
NDC: 71610-669 | Form: TABLET
Manufacturer: Aphena Pharma Solutions - Tennessee, LLC
Category: otc | Type: HUMAN OTC DRUG LABEL
Date: 20250110

ACTIVE INGREDIENTS: SODIUM BICARBONATE 650 mg/1 1
INACTIVE INGREDIENTS: CROSCARMELLOSE SODIUM; CELLULOSE, MICROCRYSTALLINE; STEARIC ACID; SILICON DIOXIDE; TALC

4624 - Rugby

Drug Facts

Active ingredient (in each tablet)

Sodium bicarbonate 10 gr (650 mg)

Purpose

Antacid

Uses

relieves:

- acid indigestion
- heartburn
- sour stomach
- upset stomach associated with these symptoms

Warnings

Do not takemore than 24 tablets for adults up to 60 years of age (or 12 tablets for adults 60 yeasr of age and older) in a 24-hour period nor use the maximum dosage for more than 2 weeks, except under the advice and supervision of a physician.

Ask a doctor before use if you havea sodium restricted diet.

Ask a doctor or pharmacist before use if you aretaking a prescription drug.

Antacids may interact with certain prescription drugs.

Stop use and ask a doctor ifsymptoms last more than 2 weeks

PREGNANCY OR BREAST FEEDING

If pregnant or breast-feeding, ask a health professional before use.

Keep out of reach of children.

OVERDOSAGE

In case of accidental overdose, seek professional assistance or contact a Poison Control Center immediately.

Directions

- do not use the maximum dosage for more than 2 weeks
- tablets may be swallowed whole or dissolved in water prior to use
- adults 60 years of age and over:1-2 tablets every 4 hours, not more than 12 tablets in 24 hours
- adults under 60 years of age:1-4 tablets every 4 hours, not more than 24 tablets in 24 hours

Other information

- each tablet contains: sodium 178 mg
- store at room temperature 15º - 30º C (59º - 86º F)

Inactive ingredients

croscarmellose sodium, microcrystalline cellulose, silica, stearic acid and talc

Questions or comments?

1-800-645-2158

TAMPER EVIDENT: DO NOT USE IF IMPRINTED SAFETY SEAL UNDER CAP IS BROKEN OR MISSING

Distributed by:

Rugby Laboratories

17177 N Laurel Park Drive, Suite 233

Livonia, MI 48152

www.rugbylaboratories.com

Rev. 12/16 R-29

Repackaging Information

Please reference the How Suppliedsection listed above for a description of individual tablets. This drug product has been received by Aphena Pharma - TN in a manufacturer or distributor packaged configuration and repackaged in full compliance with all applicable cGMP regulations. The package configurations available from Aphena are listed below:

Count | 650 mg
60 | 71610-669-53
90 | 71610-669-60
180 | 71610-669-80

Store between 20°-25°C (68°-77°F). See USP Controlled Room Temperature. Dispense in a tight light-resistant container as defined by USP. Keep this and all drugs out of the reach of children.

Repackaged by:
Cookeville, TN 38506
20221018JK

PRINCIPAL DISPLAY PANEL - 650 mg

NDC 71610-669 - Sodium Bicarbonate 650 mg Tablets